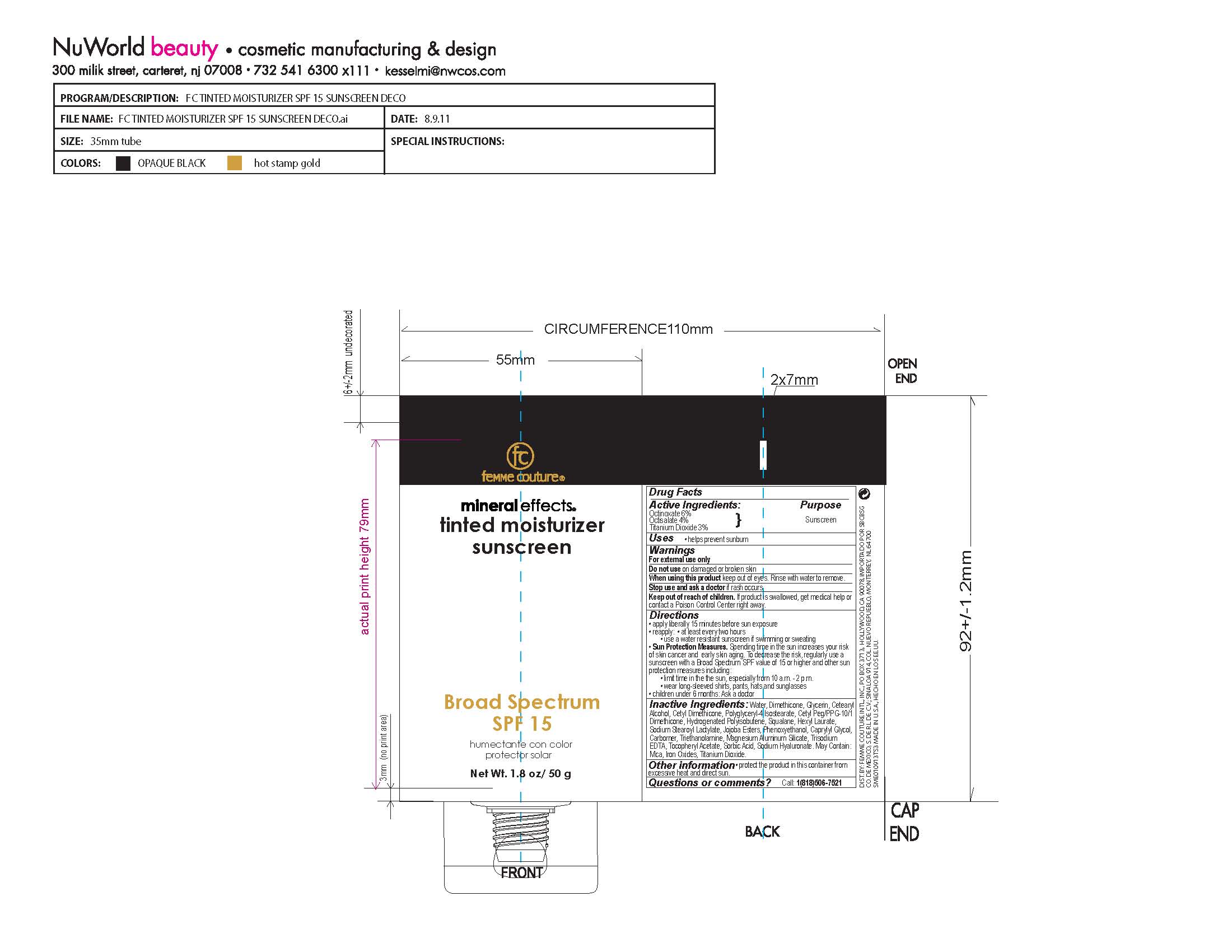 DRUG LABEL: Tinted Moisturizer 
NDC: 76351-100 | Form: CREAM
Manufacturer: Femme Couture International, Inc
Category: otc | Type: HUMAN OTC DRUG LABEL
Date: 20110603

ACTIVE INGREDIENTS: Octinoxate 3.06 g/51.03 g; Octisalate 2.04 g/51.03 g; Titanium  Dioxide 1.53 g/51.03 g
INACTIVE INGREDIENTS: Water; Carbomer 934; EDETATE TRISODIUM; Glycerin; Magnesium Aluminum Silicate; Dimethicone; Dimethicone; Cetostearyl Alcohol; Phenoxyethanol; Sorbic Acid; Caprylyl Glycol; Polyglyceryl-4 Isostearate; Dimethicone; HYDROGENATED POLYBUTENE (370 MW); Hexyl Laurate; SIMMONDSIA CHINENSIS SEED WAX; Squalane; .ALPHA.-TOCOPHEROL ACETATE, D-; SODIUM STEAROYL LACTYLATE; Trolamine; HYALURONATE SODIUM; Mica; Ferric Oxide Yellow; Ferric Oxide Red; Ferrosoferric Oxide; Brown Iron Oxide; Titanium Dioxide

ACTIVE INGREDIENT

Octinoxate 6%
Octisalate 4%
Titanium Dioxide 3%

PURPOSE

Sunscreen

WARNINGS

For external use only
Do not use on damaged or broken skin
When using this product keep out of eyes. Rinse with water to remove.
Stop use and ask a doctor if rash occurs
Keep out of reach of children. If product is swallowed, get medical help or
contact a Poison Control Center right away.

PACKAGE LABEL

a21b2c1b-2116-4fd6-b254-29f4bf1ec23f